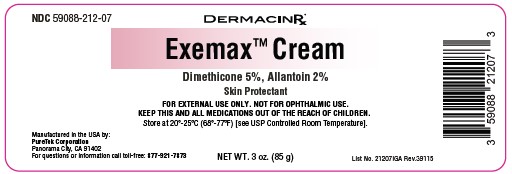 DRUG LABEL: Exemax Cream
NDC: 59088-212 | Form: CREAM
Manufacturer: PureTek Corporation
Category: otc | Type: HUMAN OTC DRUG LABEL
Date: 20250701

ACTIVE INGREDIENTS: ALLANTOIN 2 g/100 g; DIMETHICONE 5 g/100 g
INACTIVE INGREDIENTS: SIMMONDSIA CHINENSIS (JOJOBA) SEED OIL; HYALURONATE SODIUM; GINGER; CITRIC ACID; .ALPHA.-TOCOPHEROL ACETATE, DL-; ETHYLHEXYLGLYCERIN; GLYCERIN; OAT; HYDROXYETHYL ACRYLATE/SODIUM ACRYLOYLDIMETHYL TAURATE COPOLYMER (100000 MPA.S AT 1.5%); PHENOXYETHANOL; WATER; CALCIUM PANTOTHENATE; CENTELLA ASIATICA TRITERPENOIDS; LACTIC ACID; SODIUM ASCORBYL PHOSPHATE; TETRAHEXYLDECYL ASCORBATE; NIACINAMIDE; PYRIDOXINE HCL; SODIUM HYDROXIDE; MALTODEXTRIN; POLYACRYLATE CROSSPOLYMER-6; SODIUM CITRATE; BISABOLOL; ARNICA MONTANA FLOWER; CARTHAMUS TINCTORIUS (SAFFLOWER) OLEOSOMES; ALUMINUM STARCH OCTENYLSUCCINATE; INOSITOL; SACCHARIDE ISOMERATE

59088-212 Exemax Cream

Drug Facts

Active Ingredients

Dimethicone 5%
Allantoin 2%

Purpose

Skin Protectant

Uses

● temporarily protects and helps relieve chapped or cracked skin
● helps protect from the drying effects of wind and cold weather

Warnings

● For external use only

When using this product

● do not get into eyes.

Stop use and ask a doctor if

● condition worsens

● symptoms last more than 7 days or clear up and occur again within a few days

Do not use on

● deep or puncture wounds
● animal bites
● serious burns

Keep out of reach of children.

If swallowed, get medical help or contact a Poison Control Center right away.

Directions

● apply as needed

Other information

● Store at 20º-25ºC (68º-77ºF) [see USP Controlled Room Temperature]

Inactive ingredients:

Aqua (Purified Water), Arnica Montana (Arnica) Flower Extract, Avena sativa (Oat) Kernel Flour, Bisabolol, Calcium Pantothenate (Vitamin B5), Carthamus tinctorius (Safflower) Oleosomes, Centella Asiatica (Asiatic Pennywort) Extract, Citric Acid, DL-Alpha-Tocopheryl Acetate (Vitamin E), Ethylhexylglycerin, Glycerin, Hydroxyethyl Acrylate/Sodium Acryloyldimethyl Taurate Copolymer, Inositol, Lactic Acid, Maltodextrin, Niacinamide (Vitamin B3), Phenoxyethanol, Polyacrylate Crosspolymer-6, Pyridoxine HCl (Vitamin B6), Saccharide Isomerate, Simmondsia Chinensis (Jojoba) Seed Oil, Sodium Ascorbyl Phosphate (Vitamin C), Sodium Citrate, Sodium Hyaluronate, Sodium Hydroxide, Sodium Starch Octenylsuccinate, Tetrahexyldecyl Ascorbate, Zingiber Officinale (Ginger) Root Extract.

Exemax™ Cream

Manufactured by:
PureTek Corporation
Panorama City, CA 91402
For questions or information
call toll-free: 877-921-7873